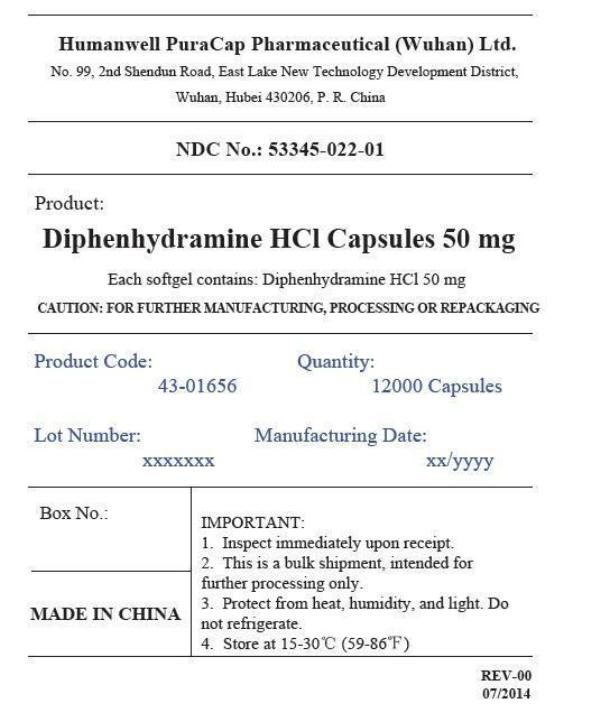 DRUG LABEL: DIPHENHYDRAMINE HYDROCHLORIDE
NDC: 53345-022 | Form: CAPSULE, LIQUID FILLED
Manufacturer: Humanwell PuraCap Pharmaceutical (Wuhan), Ltd.
Category: otc | Type: HUMAN OTC DRUG LABEL
Date: 20241125

ACTIVE INGREDIENTS: DIPHENHYDRAMINE HYDROCHLORIDE 50 mg/1 1
INACTIVE INGREDIENTS: FD&C BLUE NO. 1; GELATIN; GLYCERIN; POLYETHYLENE GLYCOL, UNSPECIFIED; WATER; SORBITOL

DIPHENHYDRAMINE HYDROCHLORIDE capsules, liquid filled

Drug Facts

Active ingredient (in each softgel)

Diphenhydramine HCl 50 mg

Purpose

Nighttime sleep-aid

Uses

- for the relief of occasional sleeplessness

Warnings

Do not use

- for children under 12 years of age
- with any other product containing diphenhydramine, even one used on skin

Ask a doctor before use if you have

- a breathing problem such as asthma, emphysema, or chronic bronchitis
- glaucoma
- trouble urinating due to an enlarged prostate gland

Ask a doctor or pharmacist before use if you aretaking sedatives or tranquilizers

When using this product

avoid alcoholic drinks

Stop use and ask a doctor ifsleeplessness persists continuously for more than 2 weeks. Insomnia may be a symptom of serious underlying medical illness.

PREGNANCY OR BREAST FEEDING

If pregnant or breast-feeding,ask a health professional before use.

Keep out of reach of children.In case of overdose, get medical help or contact a Poison Control Center right away.

Directions

- adults and children 12 years of age and over: take 1 softgel (50 mg) at bedtime if needed, or as directed by adoctor

Other information

- store at 15°-30°C (59°-86°F)

Inactive ingredients

FD&C blue #1, gelatin, glycerin, polyethylene glycol, purified water, sorbitol special and white edible ink

Manufactured by:
Humanwell PuraCap Pharmaceutical (Wuhan) Ltd.
Wuhan, Hubei 430206,
China

PRINCIPAL DISPLAY PANEL - Shipping Label

DIPHENHYDRAMINE HYDROCHLORIDE CAPSULES, 50 mg

Quantity : 12000 Capsules
NDC. No : 53345-022-01

IMPORTANT:

Inspect immediately upon receipt.
This is a bulk shipment, intended for further processing only.
Protect from heat, humidity, and light. Do not refrigerate.
Store at 15-30°C (59-86°F)
CAUTION : "FOR FURTHER MANUFACTURING, PROCESSING OR REPACKAGING"